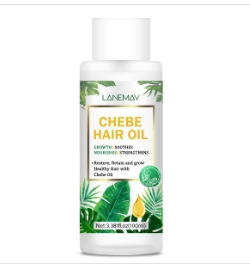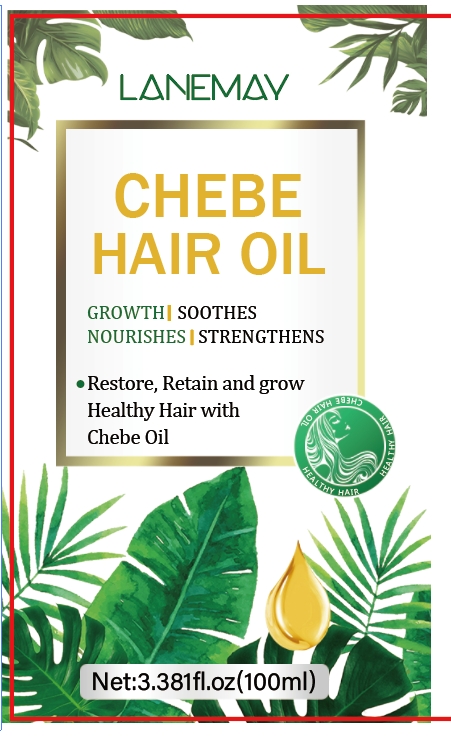 DRUG LABEL: Chebe Hair Oil
NDC: 84025-065 | Form: LIQUID
Manufacturer: Guangzhou Yanxi Biotechnology Co., Ltd
Category: otc | Type: HUMAN OTC DRUG LABEL
Date: 20240711

ACTIVE INGREDIENTS: 1,2-BUTANEDIOL 5 g/100 mL; ALLANTOIN 3 g/100 mL
INACTIVE INGREDIENTS: WATER

DOSAGE AND ADMINISTRATION

Use as a regular hair oil

WARNINGS

Keep out of Children

INACTIVE INGREDIENT

Aqua

INDICATIONS AND USAGE

Use as a regular hair oil

Keep out of Children

PURPOSE

Can repair and grow hair